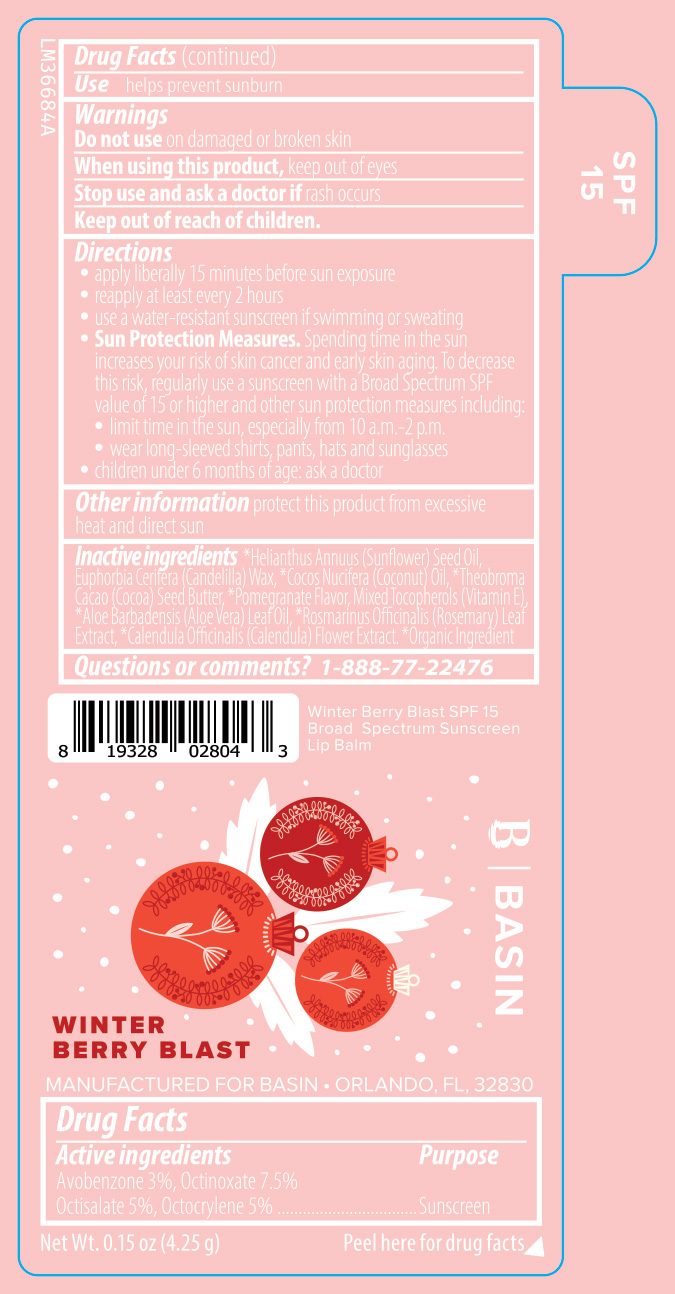 DRUG LABEL: Basin Winter Berry Blast SPF15 Broad Spectrum Sunscreen Lip Balm
NDC: 84603-118 | Form: STICK
Manufacturer: Retail Concepts of Minnesota, Inc.
Category: otc | Type: HUMAN OTC DRUG LABEL
Date: 20250728

ACTIVE INGREDIENTS: OCTINOXATE 7.5 g/100 g; AVOBENZONE 3 g/100 g; OCTOCRYLENE 5 g/100 g; OCTISALATE 5 g/100 g
INACTIVE INGREDIENTS: ROSEMARY; COCOA BUTTER; ALOE VERA LEAF; TOCOPHEROL; CALENDULA OFFICINALIS FLOWER; SUNFLOWER OIL; CANDELILLA WAX; COCONUT OIL

Basin 118S Winter Berry Blast Vegan Pomegranate SPF 15 Broad Spectrum Sunscreen Lip Balm

Active ingredients

Avobenzone 3%, Octinoxate 7.5%

Octisalate 5%, Octocrylene 5%

Purpose

Sunscreen

INDICATIONS AND USAGE

Usehelps prevent sunburn

DOSAGE AND ADMINISTRATION

Direction

- apply liberally 15 minutes before sun exposure
- reapply at least every 2 hours
- use a water resistance sunscreen if swimming or sweating
- Sun Protection MeasuresSpending time in the sun increases your risk of skin cancer and early skin aging. To decrease this risk, regularly use a sunscreen with a Broad Spectrum SPF value of 15 or higher and other sun protection measures including:
- limit time in the sun, especially from 10 a.m.-2 p.m.
- wear long-sleeved shirts, pants, hats, and sunglasses
- children under 6 months of age: ask a doctor

Warnings

Do not use on damaged or broken skin

When using this product, keep out of eyes

Stop use and ask a doctor if rash occurs

Keep out of reach of children.

STORAGE AND HANDLING

Other informationprotect this product from excessive heat and direct sun

INACTIVE INGREDIENT

Inactive ingredients*Helianthus Annuus (Sunflower) Seed Oil, Euphorbia Cerifera (Candelilla) Wax, *Cocos Nucifera (Coconut) Oil, *Theobroma Cacao (Cocoa) Seed Butter, *Pomegranate Flavor, Mixed Tocopherols (Vitamin E), *Aloe Barbadensis (Aloe Vera) Leaf Oil, *Rosmarinus Officinalis (Rosemary) Leaf Extract, *Calendula Officinalis (Calendula) Flower Extract. *Organic Ingredient

Questions or comments?1-888-77-22476

Winter Berry Blast SPF 15

Broad Spectrum Sunscreen

Lip Balm

WINTER

BERRY BLAST

BASIN

MANUFACTURED FOR BASIN - ORLANDO, FL, 32830

Net Wt. 0.15 oz (4.25 g) Peel here for drug facts

SPF

15